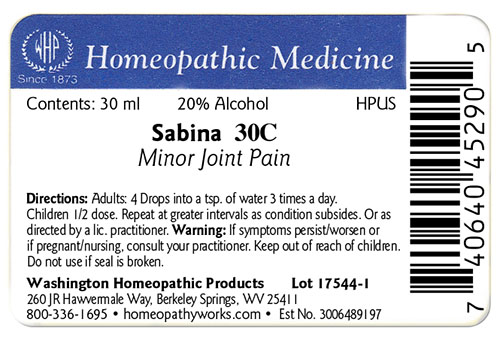 DRUG LABEL: Sabina
NDC: 71919-598 | Form: LIQUID
Manufacturer: Washington Homeopathic Products
Category: homeopathic | Type: HUMAN OTC DRUG LABEL
Date: 20250128

ACTIVE INGREDIENTS: JUNIPERUS SABINA LEAFY TWIG 30 [hp_C]/1 mL
INACTIVE INGREDIENTS: ALCOHOL; WATER

Sabina Dilution X

ACTIVE INGREDIENTS

SABINA

USES

To relieve the symptoms of minor joint pain.

KEEP OUT OF REACH OF CHILDREN

Keep this and all medicines out of reach of children.

INDICATIONS

SABINA Minor joint pain

STOP USE AND ASK DOCTOR

If symptoms persist/worsen or if pregnant/nursing, consult your practitioner.

DIRECTIONS

Adults: 4 drops into a tsp. of water 3 times a day. Children: 1/2 dose. Repeat at greater intervals as condition subsides. Or as directed bya lic. practitioner.

INACTIVE INGREDIENTS

Sucrose/Lactose

PRINCIPAL DISPLAY PANEL

The OTC potency range of SABINA is 3x–30x, 2c–30c, 200c, 1m, 10m, 50m, and CM.
Availability is subject to change.

All WHP single remedies are made to order; thus, the labels are printed on the same label stock, as the orders are filled.

‘Bottle Size,’ ‘Potency,’ and ‘Alcohol Percentage’ vary on the label depending on customer choice.

Standard bottle sizes for dilution-form remedies are 15ml, 30ml, 50ml, and 100ml.